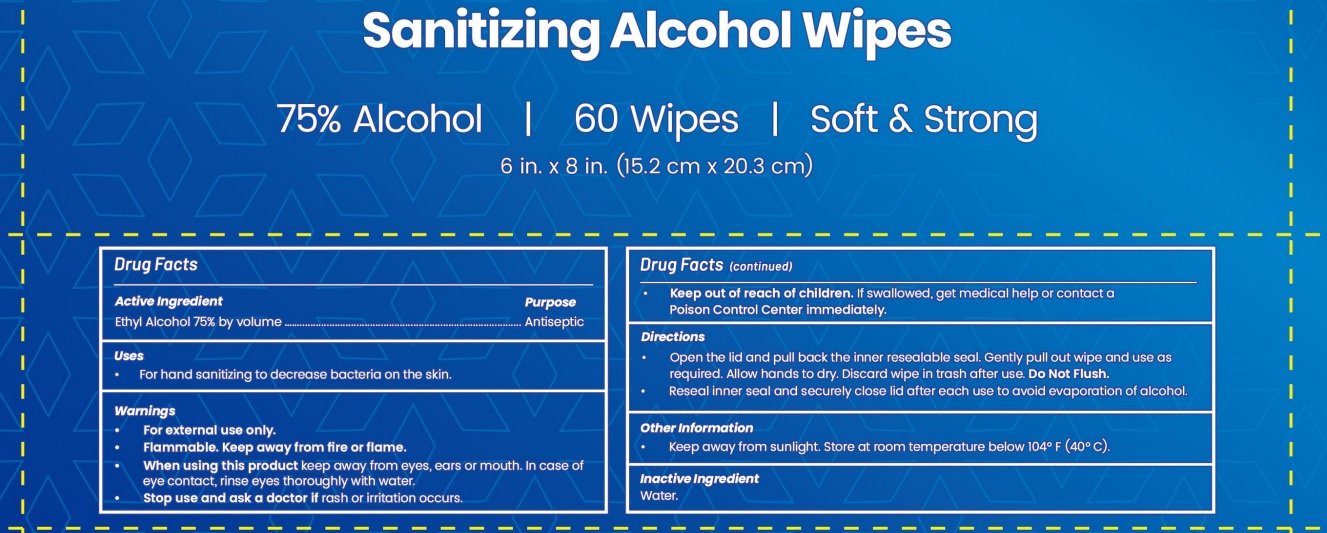 DRUG LABEL: PentaCleanse Alcohol Wipes
NDC: 82901-002 | Form: CLOTH
Manufacturer: Prestige Care Pharmacy Inc
Category: otc | Type: HUMAN OTC DRUG LABEL
Date: 20250108

ACTIVE INGREDIENTS: ALCOHOL 75 mL/100 mL
INACTIVE INGREDIENTS: WATER 25 mL/100 mL

PentaCleanse Alcohol Wipes

Active Ingredient

Ethyl Alcohol 75% by volume …….. Antiseptic

Uses

- For hand sanitizing to decrease bacteria on the skin.

WARNINGS

For external use only.

Flammable. Keep away from fire or flame.

When using this product keep away from eyes, ears or mouth. In case of eye contact, rinse eyes thoroughly with water.

Stop use and ask a doctor if rash or irritation occurs.

Keep out of reach of children. If swallowed, get medical help or contact a Poison Control Center immediately.

DOSAGE AND ADMINISTRATION

- Open the lid and pull back the inner resealable seal. Gently pull out wipe and use as required. Allow hands to dry. Discard wipe in trash after use. Do Not Flush.
- Reseal inner seal and securely close lid after each use to avoid evaporation of alcohol.

INACTIVE INGREDIENT

Water.

STORAGE AND HANDLING

- Kepp away from sunlight. Store at room temperature below 104° F (40° C).

PURPOSE

Antiseptic